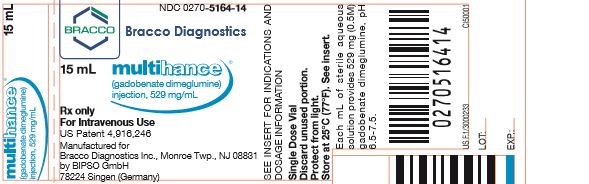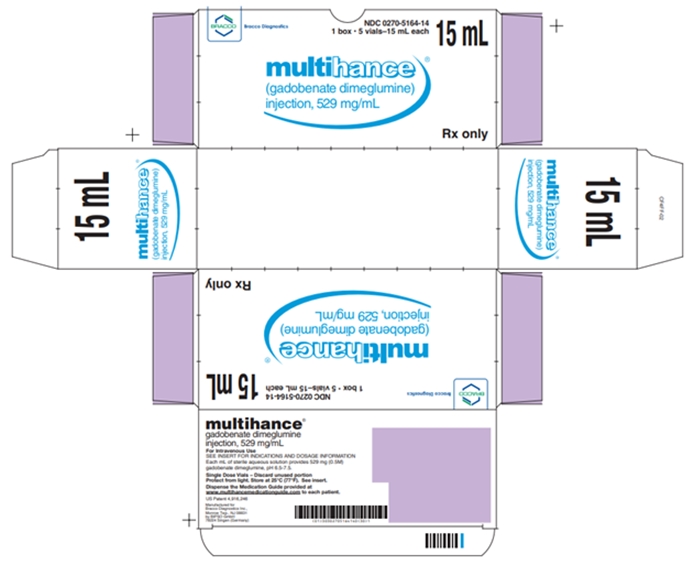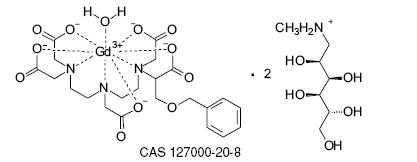 DRUG LABEL: MultiHance
NDC: 0270-5164 | Form: INJECTION, SOLUTION
Manufacturer: BRACCO DIAGNOSTICS INC
Category: prescription | Type: HUMAN PRESCRIPTION DRUG LABEL
Date: 20250314

ACTIVE INGREDIENTS: gadobenate dimeglumine 529 mg/1 mL

HIGHLIGHTS OF PRESCRIBING INFORMATION

These highlights do not include all the information needed to use MULTIHANCE safely and effectively. See full prescribing information for MULTIHANCE.
MultiHance (gadobenate dimeglumine) Injection
Initial U.S. Approval: 2004

WARNING: RISK ASSOCIATED WITH INTRATHECAL USE and NEPHROGENIC SYSTEMIC FIBROSIS

See full prescribing information for complete boxed warning

- Intrathecal administration of gadolinium based contrast agents (GBCAs) can cause serious adverse reactions including death, coma, encephalopathy, and seizures. MultiHance is not approved for intrathecal use. (5.1)
- GBCAs increase the risk for nephrogenic systemic fibrosis (NSF) among patients with impaired elimination of the drugs. Avoid use of MultiHance in these patients unless the diagnostic information is essential and not available with non-contrast MRI or other modalities. The risk for NSF appears highest among patients with:
  - chronic, severe kidney disease (GFR <30 mL/min/1.73m^2), or
  - acute kidney injury.
  Screen patients for acute kidney injury and other conditions that may reduce renal function. For patients at risk for chronically reduced renal function (e.g. age >60 years, hypertension or diabetes), estimate the glomerular filtration rate (GFR) through laboratory testing. (5.2)

1 INDICATIONS AND USAGE

- magnetic resonance imaging (MRI) of the central nervous system (CNS) in adults and pediatric patients (including term neonates), to visualize lesions with abnormal blood-brain barrier or abnormal vascularity of the brain, spine, and associated tissues. (1.1)
- magnetic resonance angiography (MRA) to evaluate adults with known or suspected renal or aorto-ilio-femoral occlusive vascular disease. (1.2)

2 DOSAGE AND ADMINISTRATION

- The recommended dose of MultiHance is 0.2 mL/kg (0.1 mmol/kg) administered as a rapid bolus intravenous injection.
- For MRI of the CNS in pediatric patients below 2 years of age the recommended dosage range is 0.1 to 0.2 mL/kg.
- To ensure complete injection of the contrast medium, follow the injection with a saline flush of at least 5 mL in MRI of the CNS and at least 20 mL in MRA. (2)

3 DOSAGE FORMS AND STRENGTHS

Each mL of MultiHance Injection contains 529 mg gadobenate dimeglumine and is available in single use vials. (3)

4 CONTRAINDICATIONS

MultiHance is contraindicated in patients with known allergic or hypersensitivity reactions to gadolinium-based contrast agents. (4)

5 WARNINGS AND PRECAUTIONS

- Hypersensitivity: anaphylactic/anaphylactoid reactions with cardiovascular, respiratory and cutaneous manifestations, ranging from mild to severe reactions including shock can occur. Monitor patients closely for need of emergency cardiorespiratory support. (5.3)
- Gadolinium is retained for months or years in brain, bone, and other organs. (5.4)

6 ADVERSE REACTIONS

The most commonly reported adverse reactions are nausea (1.3%) and headache (1.2%). (6)

To report SUSPECTED ADVERSE REACTIONS, contact Bracco Diagnostics Inc. at 1-800-257-5181 or FDA at 1-800-FDA-1088 or www.fda.gov/medwatch

8 USE IN SPECIFIC POPULATIONS

Pregnancy: Use only if imaging is essential during pregnancy and cannot be delayed. (8.1)

FULL PRESCRIBING INFORMATION

WARNING: RISK ASSOCIATED WITH INTRATHECAL USE and NEPHROGENIC SYSTEMIC FIBROSIS

Risk Associated with Intrathecal Use
Intrathecal administration of gadolinium-based contrast agents (GBCAs) can cause serious adverse reactions including death, coma, encephalopathy, and seizures. MultiHance is not approved for intrathecal use [see Warnings and Precautions (5.1)].

Nephrogenic Systemic Fibrosis
GBCAs increase the risk for nephrogenic systemic fibrosis (NSF) among patients with impaired elimination of the drugs. Avoid use of MultiHance in these patients unless the diagnostic information is essential and not available with non-contrasted MRI or other modalities. NSF may result in fatal or debilitating systemic fibrosis affecting the skin, muscle and internal organs.

The risk for NSF appears highest among patients with:

- chronic, severe kidney disease (GFR <30 mL/min/1.73m^2), or
- acute kidney injury.

Screen patients for acute kidney injury and other conditions that may reduce renal function. For patients at risk for chronically reduced renal function (e.g. age > 60 years, hypertension or diabetes), estimate the glomerular filtration rate (GFR) through laboratory testing.

For patients at highest risk for NSF, do not exceed the recommended MultiHance dose and allow a sufficient period of time for elimination of the drug from the body prior to re-administration [see Warnings and Precautions (5.2)].

1 INDICATIONS AND USAGE

1.1 Magnetic Resonance Imaging (MRI) of the Central Nervous System (CNS)

MultiHance is indicated for intravenous use in magnetic resonance imaging (MRI) of the central nervous system (CNS) in adults and pediatric patients (including term neonates), to visualize lesions with abnormal blood-brain barrier or abnormal vascularity of the brain, spine, and associated tissues.

1.2 Magnetic Resonance Angiography (MRA) of Renal and Aorto-ilio-femoral Vessels

MultiHance is indicated for use in magnetic resonance angiography (MRA) to evaluate adults with known or suspected renal or aorto-ilio-femoral occlusive vascular disease.

2 DOSAGE AND ADMINISTRATION

2.1 Dosing and Imaging Instructions

2.1.1 MRI of the CNS

In adults and in pediatric patients over 2 years of age, the recommended dose of MultiHance for MRI of the CNS is 0.2 mL/kg (0.1 mmol/kg) administered as a rapid bolus intravenous injection. In pediatric patients below 2 years of age, the recommended dosage range is 0.1 to 0.2 mL/kg administered as a rapid bolus intravenous injection. To ensure complete injection of the contrast medium, follow the injection with a saline flush of at least 5 mL. Imaging of the CNS can be performed starting immediately after the bolus injection of MultiHance.

2.1.2 MRA of Renal and Aorto-ilio-femoral Vessels

For MRA examination, the recommended dose is 0.2 mL/kg (0.1 mmol/kg) administered as a rapid bolus intravenous injection followed by at least 20 mL saline flush either manually or using an automatic injector system. Start imaging immediately after the administration of MultiHance, with scan delay calculated by test bolus or automatic bolus detection technique. If an automatic contrast detection pulse sequence is not used for bolus timing, then a test bolus injection of 1-2 mL of MultiHance should be used to calculate the appropriate scan delay.

2.2 Dosing Table

TABLE 1: WEIGHT-BASED DOSING VOLUMES FOR:
CNS IMAGING (ADULTS AND PEDIATRICS ≥2 YEARS OF AGE*)
AND
MRA IMAGING (ADULTS ONLY)
 |  | 0.1mM/kg dose
Kilograms (Kg) | Pounds (lb) | Volume, Milliliters (mL)
2.5 | 5.5 | 0.5
5 | 11 | 1.0
10 | 22 | 2.0
15 | 33 | 3.0
20 | 44 | 4.0
25 | 55 | 5.0
30 | 66 | 6.0
35 | 77 | 7.0
40 | 88 | 8.0
45 | 99 | 9.0
50 | 110 | 10.0
55 | 121 | 11.0
60 | 132 | 12.0
65 | 143 | 13.0
70 | 154 | 14.0
75 | 165 | 15.0
80 | 176 | 16.0
85 | 187 | 17.0
90 | 198 | 18.0
95 | 209 | 19.0
100 | 220 | 20.0
105 | 231 | 21.0
110 | 242 | 22.0
115 | 253 | 23.0
120 | 264 | 24.0
125 | 275 | 25.0
130 | 286 | 26.0
135 | 297 | 27.0
140 | 308 | 28.0
145 | 319 | 29.0
150 | 330 | 30.0
*For pediatric patients less than 2 years of age, one-half of the per kg dose may be used.

2.3 Administration

Inspect the MultiHance vial visually for particulate matter and discoloration prior to administration. Do not use the solution if it is discolored or particulate matter is present. Draw MultiHance into a syringe and inject using sterile technique.

Do not mix intravenous medications or parenteral nutrition solutions with MultiHance. Do not administer other medications in the same intravenous line with MultiHance.

MultiHance vials are intended for single use only. Administer immediately after opening and discard any unused product.

3 DOSAGE FORMS AND STRENGTHS

MultiHance is a sterile, nonpyrogenic, clear, colorless to slightly yellow aqueous solution for intravenous use only, containing 529 mg gadobenate dimeglumine per mL.

4 CONTRAINDICATIONS

MultiHance is contraindicated in patients with known allergic or hypersensitivity reactions to gadolinium-based contrast agents [see Warnings and Precautions (5.3)].

5 WARNINGS AND PRECAUTIONS

5.1 Risk Associated with Intrathecal Use

Intrathecal administration of GBCAs can cause serious adverse reactions including death, coma, encephalopathy, and seizures. The safety and effectiveness of MultiHance have not been established with intrathecal use. MultiHance is not approved for intrathecal use [see Dosage and Administration (2.1)].

5.2 Nephrogenic Systemic Fibrosis

GBCAs increase the risk for nephrogenic systemic fibrosis (NSF) among patients with impaired elimination of the drugs. Avoid use of MultiHance among these patients unless the diagnostic information is essential and not available with non-contrast enhanced MRI or other modalities. The GBCA-associated NSF risk appears highest for patients with chronic, severe kidney disease (GFR <30 mL/min/1.73m^2) as well as patients with acute kidney injury. The risk appears lower for patients with chronic, moderate kidney disease (GFR 30-59 mL/min/1.73m^2) and little, if any, for patients with chronic, mild kidney disease (GFR 60-89 mL/min/1.73m^2). NSF may result in fatal or debilitating fibrosis affecting the skin, muscle and internal organs. Report any diagnosis of NSF following MultiHance administration to Bracco Diagnostics (1-800-257-5181) or FDA (1-800-FDA-1088 or www.fda.gov/medwatch).

Screen patients for acute kidney injury and other conditions that may reduce renal function. Features of acute kidney injury consist of rapid (over hours to days) and usually reversible decrease in kidney function, commonly in the setting of surgery, severe infection, injury or drug-induced kidney toxicity. Serum creatinine levels and estimated GFR may not reliably assess renal function in the setting of acute kidney injury. For patients at risk for chronically reduced renal function (e.g., age >60 years, diabetes mellitus or chronic hypertension), estimate the GFR through laboratory testing.

Among the factors that may increase the risk for NSF are repeated or higher than recommended doses of a GBCA and the degree of renal impairment at the time of exposure. Record the specific GBCA and the dose administered to a patient. For patients at highest risk for NSF, do not exceed the recommended MultiHance dose and allow a sufficient period of time for elimination of the drug prior to re-administration. For patients receiving hemodialysis, physicians may consider the prompt initiation of hemodialysis following the administration of a GBCA in order to enhance the contrast agent’s elimination. The usefulness of hemodialysis in the prevention of NSF is unknown [see Dosage and Administration (2) and Clinical Pharmacology (12)].

5.3 Hypersensitivity Reactions

Anaphylactic and anaphylactoid reactions have been reported, involving cardiovascular, respiratory, and/or cutaneous manifestations. Some patients experienced circulatory collapse and died. In most cases, initial symptoms occurred within minutes of MultiHance administration and resolved with prompt emergency treatment.

Prior to MultiHance administration, ensure the availability of personnel trained and medications to treat hypersensitivity reactions. If such a reaction occurs stop MultiHance and immediately begin appropriate therapy. Additionally, consider the risk for hypersensitivity reactions, especially in patients with a history of hypersensitivity reactions or a history of asthma or other allergic disorders. Observe patients for signs and symptoms of a hypersensitivity reaction during and for up to 2 hours after MultiHance administration.

5.4 Gadolinium Retention

Gadolinium is retained for months or years in several organs. The highest concentrations (nanomoles per gram of tissue) have been identified in the bone, followed by other organs (e.g. brain, skin, kidney, liver, and spleen). The duration of retention also varies by tissue and is longest in bone. Linear GBCAs cause more retention than macrocyclic GBCAs. At equivalent doses, gadolinium retention varies among the linear agents with Omniscan (gadodiamide) and Optimark (gadoversetamide) causing greater retention than other linear agents [Eovist (gadoxetate disodium), Magnevist (gadopentetate dimeglumine), MultiHance (gadobenate dimeglumine)]. Retention is lowest and similar among the macrocyclic GBCAs [Dotarem (gadoterate meglumine), Gadavist (gadobutrol), ProHance (gadoteridol)].

Consequences of gadolinium retention in the brain have not been established. Pathologic and clinical consequences of GBCA administration and retention in skin and other organs have been established in patients with impaired renal function [see Warnings and Precautions (5.2)]. There are rare reports of pathologic skin changes in patients with normal renal function. Adverse events involving multiple organ systems have been reported in patients with normal renal function without an established causal link to gadolinium retention [see Adverse Reactions (6.2)].

While clinical consequences of gadolinium retention have not been established in patients with normal renal function, certain patients might be at higher risk. These include patients requiring multiple lifetime doses, pregnant and pediatric patients, and patients with inflammatory conditions. Consider the retention characteristics of the agent when choosing a GBCA for these patients. Minimize repetitive GBCA imaging studies, particularly closely spaced studies when possible.

5.5 Acute Renal Failure

In patients with renal insufficiency, acute renal failure requiring dialysis or worsening renal function have occurred with the use of gadolinium-based contrast agents. The risk of renal failure may increase with increasing dose of the contrast agent. Screen all patients for renal dysfunction by obtaining a history and/or laboratory tests. Consider follow-up renal function assessments for patients with a history of renal dysfunction.

5.6 Extravasation and Injection Site Reactions

Extravasation of MultiHance may lead to injection site reactions, characterized by local pain or burning sensation, swelling, blistering, and necrosis. In animal experiments, local reactions including eschar and necrosis were noted even on Day 8 post perivenous injection of MultiHance. Exercise caution to avoid local extravasation during intravenous administration of MultiHance. If extravasation occurs, evaluate and treat as necessary if local reactions develop.

5.7 Cardiac Arrhythmias

Cardiac arrhythmias have been observed in patients receiving MultiHance in clinical trials [see Adverse Reactions (6.1)]. Assess patients for underlying conditions or medications that predispose to arrhythmias.

A double-blind, placebo-controlled, 24-hour post dose continuous monitoring, crossover study in 47 subjects evaluated the effect of 0.2 mmol/kg MultiHance on ECG intervals, including QTc. The average changes in QTc values compared with placebo were minimal (<5 msec). QTc prolongation between 30 and 60 msec were noted in 20 subjects who received MultiHance vs. 11 subjects who received placebo. Prolongations ≥61 msec were noted in 6 subjects who received MultiHance and in 3 subjects who received placebo. None of these subjects had associated malignant arrhythmias. The effects on QTc by MultiHance dose, other drugs, and medical conditions were not systematically studied.

5.8 Interference with Visualization of Certain Lesions

Certain lesions seen on non-contrast images may not be seen on contrast- images. Exercise caution when interpreting contrast MR images in the absence of companion non-contrast MR images.

6 ADVERSE REACTIONS

The following adverse reactions are discussed in greater detail in other sections of the label:

- Nephrogenic systemic fibrosis [see Warnings and Precautions (5.2)]
- Hypersensitivity reactions [see Warnings and Precautions (5.3)]

6.1 Clinical Trials Experience

Because clinical trials are conducted under widely varying conditions, adverse reaction rates observed in the clinical trials of a drug cannot be directly compared to rates in the clinical trials of another drug and may not reflect the rates observed in practice.

Adults

In clinical trials with MultiHance, a total of 4967 adult subjects (137 healthy volunteers and 4830 patients) received MultiHance at doses ranging from 0.005 to 0.4 mmol/kg. There were 2838 (57%) men and 2129 (43%) women with a mean age of 56.5 years (range 18 to 93 years). A total of 4403 (89%) subjects were Caucasian, 134 (3%) Black, 275 (6%) Asian, 40 (1%) Hispanic, 70 (1%) in other racial groups, and for 45 (1%) subjects, race was not reported.

The most commonly reported adverse reactions in adult subjects who received MultiHance were nausea (1.3%) and headache (1.2%). Most adverse reactions were mild to moderate in intensity. One subject experienced a serious anaphylactoid reaction with laryngeal spasm and dyspnea [see Warnings and Precautions (5.3)]. Serious adverse reactions consisting of convulsions, pulmonary edema, acute necrotizing pancreatitis, and anaphylactoid reactions were reported in 0.1% of subjects in clinical trials.

Adverse reactions that occurred in at least 0.5% of 4967 adult subjects who received MultiHance are listed below (Table 2), in decreasing order of occurrence within each system.

TABLE 2: ADVERSE REACTIONS REPORTED IN ≥ 0.5% OF ADULT SUBJECTS WHO RECEIVED MULTIHANCE IN CLINICAL TRIALS
Number of subjects dosed | 4967
Number of subjects with any adverse reaction | 517 (10.4%)
Gastrointestinal Disorders Nausea | 67 (1.3%)
General Disorders and Administration Site Disorders Injection Site Reaction Feeling Hot | 54 (1.1%) 49 (1.0%)
Nervous System Disorders Headache Dysgeusia Paresthesia Dizziness | 60 (1.2%) 33 (0.7%) 24 (0.5%) 24 (0.5%)

The following adverse reactions occurred in less than 0.5% of the 4967 adult subjects who received MultiHance. Serious adverse reactions described above are not repeated below.
Blood and Lymphatic System Disorders: Basophilia;
Cardiac Disorders: Atrioventricular block first degree;
Eye Disorders: Eye pruritus, eye swelling, ocular hyperemia, visual disturbance;
Gastrointestinal Disorders: Abdominal pain or discomfort, diarrhea, dry mouth, lip swelling, paresthesia oral, tongue edema, vomiting;
General Disorders and Administration Site Conditions: Chest pain or discomfort, chills, malaise;
Immune System Disorders: Hypersensitivity;
Investigations: Nonspecific changes in laboratory tests (including hematology, blood chemistry, liver enzymes and urinalysis), blood pressure and electrocardiogram parameters (including PR, QRS and QT intervals and ST-T segment changes).
Musculoskeletal and Connective Tissue Disorders: Myalgia;
Nervous System Disorders: Parosmia, tremor;
Respiratory, Thoracic and Mediastinal Disorders: Dyspnea, laryngospasm, nasal congestion, sneezing, wheezing;
Skin and Subcutaneous Tissue Disorders: Hyperhidrosis, pruritus, rash, swelling face, urticaria.

Pediatric Patients

In clinical trials of MultiHance in MRI of the CNS, 307 pediatric subjects received MultiHance at a dose of 0.1 mmol/kg. A total of 160 (52%) subjects were male and the overall mean age was 6.0 years (range, 2 days to 17 years). A total of 211 (69%) subjects were Caucasian, 24 (8%) Black, 15 (5%) Asian, 39 (13%), Hispanic, 2 (<1%) in other racial groups, and for 16 (5%), race was not reported.

Adverse reactions were reported for 14 (4.6%) of the subjects. The frequency and the nature of the adverse reactions were similar to those seen in the adult patients. The most commonly reported adverse reactions were vomiting (1.0%), pyrexia (0.7%), and hyperhidrosis (0.7%). No subject died during study participation.

6.2 Postmarketing Experience

The following adverse reactions have been identified during post approval use of MultiHance or other GBCAs. Because these reactions are reported voluntarily from a population of uncertain size, it is not always possible to reliably estimate their frequency or establish a causal relationship to drug exposure.

Gastrointestinal Disorders: Acute pancreatitis with onset within 48 hours after GBCA administration.

Immune System Disorders: Anaphylactic, anaphylactoid and hypersensitivity reactions manifested with various degrees of severity up to anaphylactic shock, loss of consciousness and death. The reactions generally involved signs or symptoms of respiratory, cardiovascular, and/or mucocutaneous abnormalities.

General Disorders and Administration Site Conditions: Extravasation of MultiHance may lead to injection site reactions, characterized by local pain or burning sensation, swelling, blistering, and necrosis [see Warnings and Precautions (5.5)].

Adverse events with variable onset and duration have been reported after GBCA administration [see Warnings and Precautions (5.4)]. These include fatigue, asthenia, pain syndromes, and heterogeneous clusters of symptoms in the neurological, cutaneous, and musculoskeletal systems.

Respiratory, Thoracic and Mediastinal Disorders: Acute respiratory distress syndrome, pulmonary edema

Skin: Gadolinium associated plaques.

7 DRUG INTERACTIONS

7.1 Transporter-Based Drug-Drug Interactions

MultiHance and other drugs may compete for the canalicular multispecific organic anion transporter (MOAT also referred to as MRP2 or ABCC2). Therefore MultiHance may prolong the systemic exposure of drugs such as cisplatin, anthracyclines (e.g. doxorubicin, daunorubicin), vinca alkaloids (e.g. vincristine), methotrexate, etoposide, tamoxifen, and paclitaxel. In particular, consider the potential for prolonged drug exposure in patients with decreased MOAT activity (e.g. Dubin Johnson syndrome).

8 USE IN SPECIFIC POPULATIONS

8.1 Pregnancy

Risk Summary
GBCAs cross the placenta and result in fetal exposure and gadolinium retention. The human data on the association between GBCAs and adverse fetal outcomes are limited and inconclusive (see Data). In animal reproduction studies, gadobenate dimeglumine has been shown to be teratogenic in rabbits following repeated intravenous administration during organogenesis at doses up to 6 times the recommended human dose. There were no adverse developmental effects observed in rats with intravenous administration of gadobenate dimeglumine during organogenesis at doses up to three times the recommended human dose (see Data). Because of the potential risks of gadolinium to the fetus, use MultiHance only if imaging is essential and cannot be delayed.

The estimated background risk of major birth defects and miscarriage for the indicated population is unknown. All pregnancies have a background risk of birth defect, loss, or other adverse outcomes. In the U.S. general population, the estimated background risk of major birth defects and miscarriage in clinically recognized pregnancies is 2 to 4% and is 15 to 20%, respectively.

Data
Human Data
Contrast enhancement is visualized in the placenta and fetal tissues after maternal GBCA administration.

Cohort studies and case reports on exposure to GBCAs during pregnancy have not reported a clear association between GBCAs and adverse effects in the exposed neonates. However, a retrospective cohort study, comparing pregnant women who had a GBCA MRI to pregnant women who did not have an MRI, reported a higher occurrence of stillbirths and neonatal deaths in the group receiving GBCA MRI. Limitations of this study include a lack of comparison with non-contrast MRI and lack of information about the maternal indication for MRI. Overall, these data preclude a reliable evaluation of the potential risk of adverse fetal outcomes with the use of GBCAs in pregnancy.

Animal Data
Gadolinium Retention
GBCAs administered to pregnant non-human primates (0.1 mmol/kg on gestational days 85 and 135) result in measurable gadolinium concentration in the offspring in bone, brain, skin, liver, kidney, and spleen for at least 7 months. GBCAs administered to pregnant mice (2 mmol/kg daily on gestational days 16 through 19) result in measurable gadolinium concentrations in the pups in bone, brain, kidney, liver, blood, muscle, and spleen at one month postnatal age.
Reproductive Toxicology
Gadobenate dimeglumine has been shown to be teratogenic in rabbits when administered intravenously at 2 mmol/kg/day (6 times the recommended human dose based on body surface area) during organogenesis (day 6 to 18) inducing microphthalmia/small eye and/or focal retinal fold in 3 fetuses from 3 separate litters. In addition, MultiHance administered intravenously at 3 mmol/kg/day (10 times the recommended human dose based on body surface area) has been shown to increase intrauterine deaths in rabbits. There was no evidence that MultiHance induced teratogenic effects in rats at doses up to 2 mmol/kg/day (3 times the recommended human dose based on body surface area), however, rat dams exhibited no systemic toxicity at this dose. There were no adverse effects on the birth, survival, growth, development and fertility of the F1 generation at doses up to 2 mmol/kg in a rat peri- and post-natal (Segment III) study.

8.2 Lactation

Risk Summary
Limited literature reports that breastfeeding after gadobenate dimeglumine administration to the mother would result in the infant receiving an oral dose of 0.001%-0.04% of the maternal dose. There is no information on the effects of the drug on the breastfed infant or the effects of the drug on milk production. Additionally, there is limited GBCA gastrointestinal absorption. The developmental and health benefits of breastfeeding should be considered together with the mother’s clinical need for MultiHance and any potential adverse effects on the breastfed infant from MultiHance or from the underlying maternal condition.

8.4 Pediatric Use

MultiHance is approved for intravenous use for MRI of the CNS to visualize lesions with abnormal blood brain barrier or abnormal vascularity of the brain, spine, and associated tissues in pediatric patients from birth, including term neonates, to less than 17 years of age. Pediatric use is based on evidence of effectiveness in adults and in 202 pediatric patients 2 years of age and older, in addition to experience in 105 pediatric patients birth to less than 2 years of age that supported extrapolation from adult data [see Clinical Studies (14)]. Adverse reactions in pediatric patients were similar to those reported in adults [see Adverse Reactions (6.1)]. No dose adjustment according to age is necessary in pediatric patients two years of age and older. For pediatric patients, less than 2 years of age, the recommended dosage range is 0.1 to 0.2 mL/kg [see Dosage and Administration (2.1), Pharmacokinetics (12.3)]. The safety of MultiHance has not been established in preterm neonates.

8.5 Geriatric Use

Of the total number of 4967 adult subjects in clinical studies of MultiHance, 33% were 65 or older. No overall differences in safety or effectiveness were observed between these elderly subjects and the younger subjects.

The drug is known to be substantially excreted by the kidney, and the risk of toxic reactions to MultiHance may be greater in patients with impaired renal function. Because elderly patients are more likely to have decreased renal function it may be useful to monitor renal function.

10 OVERDOSAGE

Clinical consequences of overdosage with MultiHance have not been reported. Treatment of an overdosage should be directed toward support of vital functions and prompt institution of symptomatic therapy. In a Phase 1 clinical study, doses up to 0.4 mmol/kg were administered to patients. MultiHance has been shown to be dialyzable [see Clinical Pharmacology (12.3)].

11 DESCRIPTION

MultiHance injection is supplied as a sterile, nonpyrogenic, clear, colorless to slightly yellow aqueous solution intended for intravenous use only. Each mL of MultiHance contains 529 mg gadobenate dimeglumine and water for injection. MultiHance contains no preservatives.

Gadobenate dimeglumine is chemically designated as (4RS)-[4-carboxy-5,8,11-tris(carboxymethyl)- 1-phenyl-2-oxa-5,8,11-triazatridecan-13-oato(5-)] gadolinate(2-) dihydrogen compound with 1-deoxy-1-(methylamino)-D-glucitol (1:2) with a molecular weight of 1058.2 and an empirical formula of C22H28GdN3O11 • 2C7H17NO5. The structural formula is as follows:

MultiHance has a pH of 6.5-7.5. Pertinent physicochemical parameters are provided below:

Osmolality | 1.970 osmol/kg @ 37°C
Viscosity | 5.3 mPas @ 37°C
Density | 1.220 g/mL @ 20°C

MultiHance has an osmolality 6.9 times that of plasma (285 mOsmol/kg water) and is hypertonic under conditions of use.

12 CLINICAL PHARMACOLOGY

12.1 Mechanism of Action

Gadobenate dimeglumine is a paramagnetic agent and, as such, develops a magnetic moment when placed in a magnetic field. The large magnetic moment produced by the paramagnetic agent results in a large local magnetic field, which can enhance the relaxation rates of water protons in its vicinity leading to an increase of signal intensity (brightness) of tissue.

In magnetic resonance imaging (MRI), visualization of normal and pathological tissue depends in part on variations in the radiofrequency signal intensity that occur with 1) differences in proton density; 2) differences of the spin-lattice or longitudinal relaxation times (T1); and 3) differences in the spin-spin or transverse relaxation time (T2). When placed in a magnetic field, gadobenate dimeglumine decreases the T1 and T2 relaxation time in target tissues. At recommended doses, the effect is observed with greatest sensitivity in the T1-weighted sequences.

12.2 Pharmacodynamics

Unlike other tested paramagnetic contrast agents (See Table 3), MultiHance demonstrates weak and transient interactions with serum proteins that causes slowing in the molecular tumbling dynamics, resulting in strong increases in relaxivity in solutions containing serum proteins. The improved relaxation effect can contribute to increased contrast-to-noise ratio and lesion-to-brain ratio, which may improve visualization.

TABLE 3: RELAXIVITY (mM^–1s^–1) OF GADOLINIUM CHELATES
 | Human plasma
 | r1 | r2
Gadobenate | 9.7^1 | 12.5^1
Gadopentetate | 4.9^1 | 6.3^1
Gadodiamide | 5.4^2 | --
Gadoteridol | 5.4^2 | --
r1 and r2 relaxivities indicate the efficiency in shortening T1 and T2 relaxation times, respectively.
^1 In heparinized human plasma, at 39°C.
^2 In citrated human plasma, at 37°C.
-- Not available

Disruption of the blood-brain barrier or abnormal vascularity allows enhancement by MultiHance of lesions such as neoplasms, abscesses, and infarcts. Uptake of MultiHance into hepatocytes has been demonstrated.

12.3 Pharmacokinetics

Three single-dose intravenous studies were conducted in 32 healthy male subjects to assess the pharmacokinetics of gadobenate dimeglumine. The doses administered in these studies ranged from 0.005 to 0.4 mmol/kg. Upon injection, the meglumine salt is completely dissociated from the gadobenate dimeglumine complex. Thus, the pharmacokinetics is based on the assay of gadobenate ion, the MRI contrast effective ion in gadobenate dimeglumine. Data for plasma concentration and area under the curve demonstrated linear dependence on the administered dose. The pharmacokinetics of gadobenate ion following intravenous administration can be best described using a two-compartment model.

Distribution
Gadobenate ion has a rapid distribution half-life (reported as mean ± SD) of 0.084 ± 0.012 to 0.605 ± 0.072 hours. Volume of distribution of the central compartment ranged from 0.074 ± 0.017 to 0.158 ± 0.038 L/kg, and estimates of volume of distribution by area ranged from 0.170 ± 0.016 to 0.282 ± 0.079 L/kg. These latter estimates are approximately equivalent to the average volume of extracellular body water in man. In vitro studies showed no appreciable binding of gadobenate ion to human serum proteins. Following GBCA administration, gadolinium is present for months or years in brain, bone, skin, and other organs [see Warnings and Precautions (5.4)].

Elimination
Gadobenate ion is eliminated predominately via the kidneys, with 78% to 96% of an administered dose recovered in the urine. Total plasma clearance and renal clearance estimates of gadobenate ion were similar, ranging from 0.093 ± 0.010 to 0.133 ± 0.270 L/hr/kg and 0.082 ± 0.007 to 0.104 ± 0.039 L/hr/kg, respectively. The clearance is similar to that of substances that are subject to glomerular filtration. The mean elimination half-life ranged from 1.17 ± 0.26 to 2.02 ± 0.60 hours. A small percentage of the administered dose (0.6% to 4%) is eliminated via the biliary route and recovered in feces.

Metabolism
There was no detectable biotransformation of gadobenate ion. Dissociation of gadobenate ion in vivo has been shown to be minimal, with less than 1% of the free chelating agent being recovered alone in feces.

Pharmacokinetics in Special Populations

Renal Impairment: A single intravenous dose of 0.2 mmol/kg of MultiHance was administered to 20 subjects with impaired renal function (6 men and 3 women with moderate renal impairment [urine creatinine clearance >30 to <60 mL/min] and 5 men and 6 women with severe renal impairment [urine creatinine clearance >10 to <30 mL/min]). Mean estimates of the elimination half-life were 6.1 ± 3.0 and 9.5 ± 3.1 hours for the moderate and severe renal impairment groups, respectively as compared with 1.0 to 2.0 hours in healthy volunteers.

Hemodialysis: A single intravenous dose of 0.2 mmol/kg of MultiHance was administered to 11 subjects (5 males and 6 females) with end-stage renal disease requiring hemodialysis to determine the pharmacokinetics and dialyzability of gadobenate. Approximately 72% of the dose was recovered by hemodialysis over a 4-hour period. The mean elimination half-life on dialysis was 1.21 ± 0.29 hours as compared with 42.4 ± 24.4 hours when off dialysis.

Hepatic Impairment: A single intravenous dose of 0.1 mmol/kg of MultiHance was administered to 11 subjects (8 males and 3 females) with impaired liver function (Class B or C modified Child-Pugh Classification). Hepatic impairment had little effect on the pharmacokinetics of MultiHance with the parameters being similar to those calculated for healthy subjects.

Gender, Age, Race: A multiple regression analysis performed using pooled data from several pharmacokinetic studies found no significant effect of sex upon the pharmacokinetics of gadobenate. Clearance appeared to decrease slightly with increasing age. Since variations due to age appeared marginal, dosage adjustment for geriatric population is not recommended. Pharmacokinetic differences due to race have not been systematically studied.

Pediatric: A population pharmacokinetic analysis incorporated data from 25 healthy subjects (14 males and 11 females) and 15 subjects undergoing MR imaging of the central nervous system (7 males and 8 females) between ages of 2 and 16 years. The subjects received a single intravenous dose of 0.1 mmol/kg of MultiHance. The geometric mean Cmax was 62.3 μg/mL (n=16) in children 2 to 5 years of age, and 64.2 μg/mL (n=24) in children older than 5 years. The geometric mean AUC 0-∞ was 77.9 μg⋅h/mL in children 2-5 years of age (n=16) and 82.6 μg⋅h/mL in children older than 5 years (n=24). The geometric mean half-life was 1.2 hours in children 2 to 5 years of age and 0.93 hours in children older than 5 years. There was no significant gender-related difference in the pharmacokinetic parameters in the pediatric patients. Over 80% of the dose was recovered in urine after 24 hours. Pharmacokinetic simulations indicate similar AUC and Cmax values for MultiHance in pediatric subjects less than 2 years when compared to those reported for adults; no age-based dose adjustment is necessary for this pediatric population.

13 NONCLINICAL TOXICOLOGY

13.1 Carcinogenesis, Mutagenesis, Impairment of Fertility

Long-term animal studies have not been performed to evaluate the carcinogenic potential of MultiHance.

The results for MultiHance were negative in the following genetic toxicity studies: 1) in vitro bacteria reverse mutation assays, 2) an in vitro gene mutation assay in mammalian cells, 3) an in vitro chromosomal aberration assay, 4) an in vitro unscheduled DNA synthesis assay, and 5) an in vivo micronucleus assay in rats.

MultiHance had no effect on fertility and reproductive performance at IV doses of up to 2 mmol/kg/day (3 times the human dose on body surface basis) for 13 weeks in male rats and for 32 days in female rats. However, vacuolation in testes and abnormal spermatogenic cells were observed when MultiHance was intravenously administered to male rats at 3 mmol/kg/day (5 times the human dose on body surface basis) for 28 days. The effects were not reversible following 28-day recovery period. The effects were not reported in dog and monkey studies (at doses up to about 11 and 10 times the human dose on body surface basis for dogs (28 days dosing) and monkeys (14 days dosing), respectively).

14 CLINICAL STUDIES

14.1 MRI of the CNS

Adults:
MultiHance was evaluated in 426 adult patients in 2 controlled clinical trials of the central nervous system (Study A and Study B), enrolling 217 men and 209 women with a mean age of 52 years (range 18 to 88 years). The racial and ethnic representations were 88% Caucasian, 6% Black, 4% Hispanic, 1% Asian, and 1% other racial or ethnic groups. These trials were designed to compare MultiHance contrast MRI to non-contrast MRI alone. In Study A, patients highly suspected of having a lesion(s) of the CNS based on nuclear medicine imaging, computed tomography (CT), contrast CT, MRI, contrast- MRI, or angiography were randomized to receive two MRI evaluations with 0.05 mmol/kg (n=140) or 0.1 mmol/kg (n=136) of MultiHance. In Study B, patients with known metastatic disease to the CNS were randomized to receive two MRI evaluations with 0.05 mmol/kg (n=74) or 0.1 mmol/kg (n=76) of MultiHance. MRI scans were performed pre-contrast and within 5 minutes after each injection. The studies were designed to evaluate the effect of MultiHance MRI compared to the non-contrast MRI on a lesion level. Pre-contrast, post-contrast, and pre-plus-post contrast images (paired images) were independently evaluated by three blinded readers. The images were evaluated for the following endpoints using a scale from 0 to 4: the degree of lesion border delineation, the degree of visualization of lesion internal morphology, and the degree of lesion contrast enhancement. Lesion counting was also performed for the pre-contrast and paired image sets.

The 0.1 mmol/kg dose of MultiHance demonstrated consistently better visualization for all readers for all visualization endpoints. However, the 0.05 mmol/kg dose of MultiHance provided inconsistent visualization results between readers.

Comparison of pre-contrast versus post-contrast (0.1 mmol/kg) images showed that the mean score differences were significant and favored contrast for subjects in Study B (all subjects with known metastatic lesions) and for subjects with known tumors in Study A. However, the mean score differences between the pre-contrast and post-contrast images were not significant for non-tumor patients in Study A. These negative results may be attributed to a lack of lesion enhancement in non-tumor CNS disease.

Table 4 shows a comparison of paired images (pre-and post-contrast) versus pre-contrast images with respect to the difference in the mean score and with respect to the proportion of lesions read as better, worse, or the same as the pre-contrast MRI images. Table 4 shows that based on a lesion-level analysis 0.1 mmol/kg MultiHance provided a statistically significant improvement for the three structural parameters evaluated. Also, more lesions were seen in the paired images than in the pre-contrast images alone.

Table 4: LESION LEVEL RESULTS OF MRI CENTRAL NERVOUS SYSTEM ADULT STUDIES WITH 0.1 mmol/kg MULTIHANCE
 | Study A |  |  | Study B
 | Reader 1 | Reader 2 | Reader 3 | Reader 1 | Reader 2 | Reader 3
Endpoints | N = 395 | N = 384 | N = 299 | N = 245 | N = 275 | N = 254
Border Delineation:
Difference of Means (a) | 0.8* | 0.6* | 0.8* | 1.8* | 1.5* | 1.9*
Worse (b) Same Better | 44 (11%) 146 (37%) 205 (52%) | 61 (16%) 168 (44%) 155 (40%) | 57 (19%) 89 (30%) 153 (51%) | 13 (5%) 11 (5%) 221 (90%) | 24 (9%) 19 (7%) 232 (84%) | 15 (6%) 18 (7%) 221 (87%)
Internal Morphology:
Difference of Means | 0.8* | 0.6* | 0.7* | 1.7* | 1.4* | 2.1*
Worse Same Better | 37 (10%) 147 (37%) 211 (53%) | 63 (17%) 151 (39%) 170 (44%) | 62 (21%) 84 (28%) 153 (51%) | 13 (5%) 16 (7%) 216 (88%) | 26 (10%) 22 (8%) 227 (82%) | 14 (5%) 22 (9%) 218 (86%)
Contrast Enhancement:
Difference of Means | 0.7* | 0.5* | 0.8* | 1.9* | 1.3* | 1.9*
Worse Same Better | 75 (19%) 148 (37%) 172 (44%) | 74 (19%) 152 (40%) 158 (41%) | 50 (17%) 109 (36%) 140 (47%) | 13 (5%) 11 (5%) 221 (90%) | 32 (12%) 21 (7%) 222 (81%) | 17 (7%) 14 (5%) 223 (88%)
(a) Difference of means = (paired mean) - (pre mean)
(b) Worse = paired score is less than the pre score
Same = paired score is the same as the pre score
Better = paired score is greater than the pre score
* Statistically significant for the mean (paired t test)

Pediatric 2 to 17 years
The efficacy and safety of MultiHance were evaluated in 92 pediatric patients with known or highly suspected disease of the central nervous system. MRI scans were performed pre-contrast and within 3 to 10 minutes following the administration of MultiHance 0.1 mmol/kg. Pre-contrast, post-contrast, and pre-plus-post contrast images (paired images) were independently evaluated by three blinded readers on a lesion level. The images were evaluated for the same endpoints as in the adult central nervous system trials using a scale from 0 to 4: the degree of lesion border delineation, the degree of visualization of lesion internal morphology, and the degree of lesion contrast enhancement. Lesion counting was also performed for the pre-contrast and paired image sets. The pre-contrast versus the paired image set was the primary comparison. Forty-nine percent of study subjects were male and the overall mean age was 10.6 years (range 2 to 17 years). The racial and ethnic representations were 77% Caucasian, 13% Asian, 5% Black, and 4% other racial or ethnic groups. MultiHance increased lesion border delineation, lesion internal morphology, and lesion contrast enhancement relative to non-contrast and these results were comparable to those seen in adults.

Pediatrics below 2 years
A study of 90 pediatric patients younger than 2 years of age was performed which supports extrapolation of CNS efficacy findings from adults and older pediatric patients. Three independent, blinded readers evaluated pre-contrast MRI image sets and paired pre-plus-post-contrast MRI image sets using MultiHance and rated the images according to three co-primary endpoints at a lesion level for the primary analysis. Two of the three readers reported improvement in the paired image sets in each of the three co-primary endpoints of lesion border delineation, visualization of lesion internal morphology, and lesion contrast enhancement.

14.2 MRA of Renal and Aorto-ilio-femoral Vessels

Safety and efficacy of MultiHance for use in MRA were evaluated in two prospective, multi-center, open-label, clinical trials (one for each arterial vascular territory: renal and aorto-ilio-femoral). Out of 580 patients who received Multihance in these two trials, 62.2% were men and 90.9% were Caucasian; the average age was 63.4 years (range 18 to 93 years). In both trials, patients with known or suspected arterial disease underwent MRA with and without MultiHance as well as catheter-based digital subtraction angiography (DSA). Assessment of diagnostic efficacy for detecting/excluding clinically significant steno-occlusive disease (≥ 51% stenosis measured with electronic calipers) was based on comparisons of sensitivity and specificity between MultiHance MRA and non-contrast MRA, with DSA as a reference standard.

In each vascular territory, the primary efficacy analyses were designed to demonstrate superiority in sensitivity and non-inferiority in specificity of MultiHance MRA to non-contrast MRA at the vessel-segment level. The interpretation of MRA images from both trials was conducted by three independent radiologist readers who were blinded to clinical data, including the DSA results. The pre-specified success criteria were to be achieved by at least the same two readers for all primary analyses.

Results of both trials showed a statistically significant increase in sensitivity and specificity of MultiHance MRA over non-contrast MRA in detecting clinically significant steno-occlusive disease.

Table 5 summarizes the efficacy results by reader.

TABLE 5. PERFORMANCE CHARACTERISTICS OF MULTIHANCE-MRA AND NON-CONTRAST MRA
* (Based on General Delta Method)
READER | AORTO-ILIO-FEMORAL ARTERIES
READER | SENSITIVITY |  |  | SPECIFICITY
READER | MultiHance MRA [A] | Non-contrast MRA [B] | [A] – [B] (95% CI)* | MultiHance MRA [A] | Non-contrast MRA [B] | [A] – [B] (95% CI)*
1 | 77.8% | 73.7% | 4.5 (1.5, 7.6) | 88.1% | 78.5% | 10.0 (7.3, 12.6)
2 | 65.2% | 52.5% | 12.6 (8.5, 16.6) | 94.2% | 89.4% | 4.9 (2.7, 7.1)
3 | 69.0% | 59.1% | 10.0 (6.1, 14.0) | 90.0% | 75.3% | 14.9 (12.1, 17.8)
READER | RENAL ARTERIES
READER | SENSITIVITY |  |  | SPECIFICITY
READER | MultiHance MRA [A] | Non-contrast MRA [B] | [A] – [B] (95% CI)* | MultiHance MRA [A] | Non-contrast MRA [B] | [A] – [B] (95% CI)*
1 | 67.8% | 47.0% | 20.8 (12.8, 28.9) | 94.0% | 86.1% | 8.3 (4.2, 12.4)
2 | 62.4% | 46.7% | 16.2 (6.8, 25.6) | 94.0% | 83.5% | 10.3 (5.5, 15.0)
3 | 65.5% | 39.6% | 25.3 (15.9, 34.6) | 94.7% | 87.3% | 8.0 (3.6, 12.5)

16 HOW SUPPLIED/STORAGE AND HANDLING

16.1 How Supplied
MultiHance (gadobenate dimeglumine) is a clear, colorless to slightly yellow solution containing 529 mg gadobenate dimeglumine per mL. MultiHance is supplied in glass vials; each single dose vial is rubber stoppered with an aluminum seal and the contents are sterile. MultiHance is supplied in boxes of:

Five 5 mL single dose 10 mL vials              (NDC 0270-5164-12)
Five 10 mL single dose 20 mL vials           (NDC 0270-5164-13)
Five 15 mL single dose 20 mL vials           (NDC 0270-5164-14)
Five 20 mL single dose 20 mL vials           (NDC 0270-5164-15)

16.2 Storage and Handling
Store at 25°C (77°F), excursions permitted to 15-30°C (59-86°F) [see USP Controlled Room Temperature]. Do not freeze.

17 PATIENT COUNSELING INFORMATION

- Advise the patient to read the FDA-approved patient labeling (Medication Guide) found at www.multihancemedicationguide.com.

Nephrogenic Systemic Fibrosis
Instruct patients to inform their physician if they:

- have a history of kidney and/or liver disease, or
- have recently received a GBCA.

GBCAs increase the risk for NSF among patients with impaired elimination of the drugs. To counsel patients at risk for NSF:

- Describe the clinical manifestations of NSF
- Describe procedures to screen for the detection of renal impairment.

Instruct the patients to contact their physician if they develop signs or symptoms of NSF following MultiHance administration, such as burning, itching, swelling, scaling, hardening and tightening of the skin; red or dark patches on the skin; stiffness in joints with trouble moving, bending or straightening the arms, hands, legs or feet; pain in the hip bones or ribs; or muscle weakness.

Common Adverse Reactions
Inform patients that they may experience:

- reactions along the venous injection site, such as mild and transient burning or pain or feeling of warmth or coldness at the injection site
- side effects of feeling hot, nausea, and headache.

Gadolinium Retention
Advise patients that gadolinium is retained for months or years in brain, bone, skin, and other organs in patients with normal renal function. The clinical consequences of retention are unknown. Retention depends on multiple factors and is greater following administration of linear GBCAs than following administration of macrocyclic GBCAs [see Warnings and Precautions (5.4)].

Rx only
US Patent No. 4,916,246

Manufactured for
Bracco Diagnostics Inc.
Princeton, NJ 08540

By BIPSO GmbH
78224 Singen (Germany)

March 2025
CL44F-09

MEDICATION GUIDE
MULTIHANCE® (məl-tē-han(t)s)
(gadobenate dimeglumine)
Injection, for intravenous use

What is the most important information I should know about MULTIHANCE?

- GBCAs like MULTIHANCE may cause serious side effects including death, coma, encephalopathy, and seizures when it is given intrathecally (injection given into the spinal cord). It is not known if MULTIHANCE is safe and effective with intrathecal use. MULTIHANCE is not approved for this use.
- MULTIHANCE contains a metal called gadolinium. Small amounts of gadolinium can stay in your body including the brain, bones, skin and other parts of your body for a long time (several months to years).
- It is not known how gadolinium may affect you, but so far, studies have not found harmful effects in patients with normal kidneys.
- Rarely, patients have reported pains, tiredness, and skin, muscle or bone ailments for a long time, but these symptoms have not been directly linked to gadolinium.
- There are different GBCAs that can be used for your MRI exam. The amount of gadolinium that stays in the body is different for different gadolinium medicines. Gadolinium stays in the body more after Omniscan or Optimark than after Eovist, Magnevist, or MultiHance. Gadolinium stays in the body the least after Dotarem, Gadavist, or ProHance.
- People who get many doses of gadolinium medicines, women who are pregnant and young children may be at increased risk from gadolinium staying in the body.
- Some people with kidney problems who get gadolinium medicines can develop a condition with severe thickening of the skin, muscles and other organs in the body (nephrogenic systemic fibrosis). Your healthcare provider should screen you to see how well your kidneys are working before you receive MULTIHANCE.

What is MULTIHANCE?

- MULTIHANCE is a prescription medicine called a gadolinium-based contrast agent (GBCA). MULTIHANCE, like other GBCAs, is injected into your vein and used with a magnetic resonance imaging (MRI) scanner.
- An MRI exam with a GBCA, including MULTIHANCE, helps your doctor to see problems better than an MRI exam without a GBCA.
- Your doctor has reviewed your medical records and has determined that you would benefit from using a GBCA with your MRI exam.

Do not receive MULTIHANCE if you have had a severe allergic reaction to GBCAs including gadobenate dimeglumine, or any of the ingredients in MULTIHANCE.

Before receiving MULTIHANCE, tell your healthcare provider about all your medical conditions, including if you:

- have had any MRI procedures in the past where you received a GBCA. Your healthcare provider may ask you for more information including the dates of these MRI procedures.
- are pregnant or plan to become pregnant. It is not known if MULTIHANCE can harm your unborn baby. Talk to your healthcare provider about the possible risks to an unborn baby if a GBCA such as MULTIHANCE is received during pregnancy
- have kidney problems, diabetes, or high blood pressure.
- have had an allergic reaction to dyes (contrast agents) including GBCAs

What are the possible side effects of MULTIHANCE?

- See “What is the most important information I should know about MULTIHANCE?”
- Allergic reactions. MULTIHANCE can cause allergic reactions that can sometimes be serious. Your healthcare provider will monitor you closely for symptoms of an allergic reaction.

The most common side effects of MULTIHANCE include: nausea, headache, feeling hot, or burning at the injection site.
These are not all the possible side effects of MULTIHANCE.
Call your doctor for medical advice about side effects. You may report side effects to FDA at 1-800-FDA-1088.

General information about the safe and effective use of MULTIHANCE.
Medicines are sometimes prescribed for purposes other than those listed in a Medication Guide. You can ask your healthcare provider for information about MULTIHANCE that is written for health professionals.

What are the ingredients in MULTIHANCE?
Active ingredient: gadobenate dimeglumine
Inactive ingredients: water
Manufactured by: BIPSO GmbH-78224 Singen (Germany)
Manufactured for: Bracco Diagnostics Inc., Princeton, NJ 08540
US Patent No. 4,916,246
For more information, go to www.imaging.bracco.com or call 1-800-257-5181.

This Medication Guide has been approved by the U.S. Food and Drug Administration

Revised: 03/2025

PACKAGE LABEL

MultiHance® Injection 15 mL
NDC 0270–5164–14